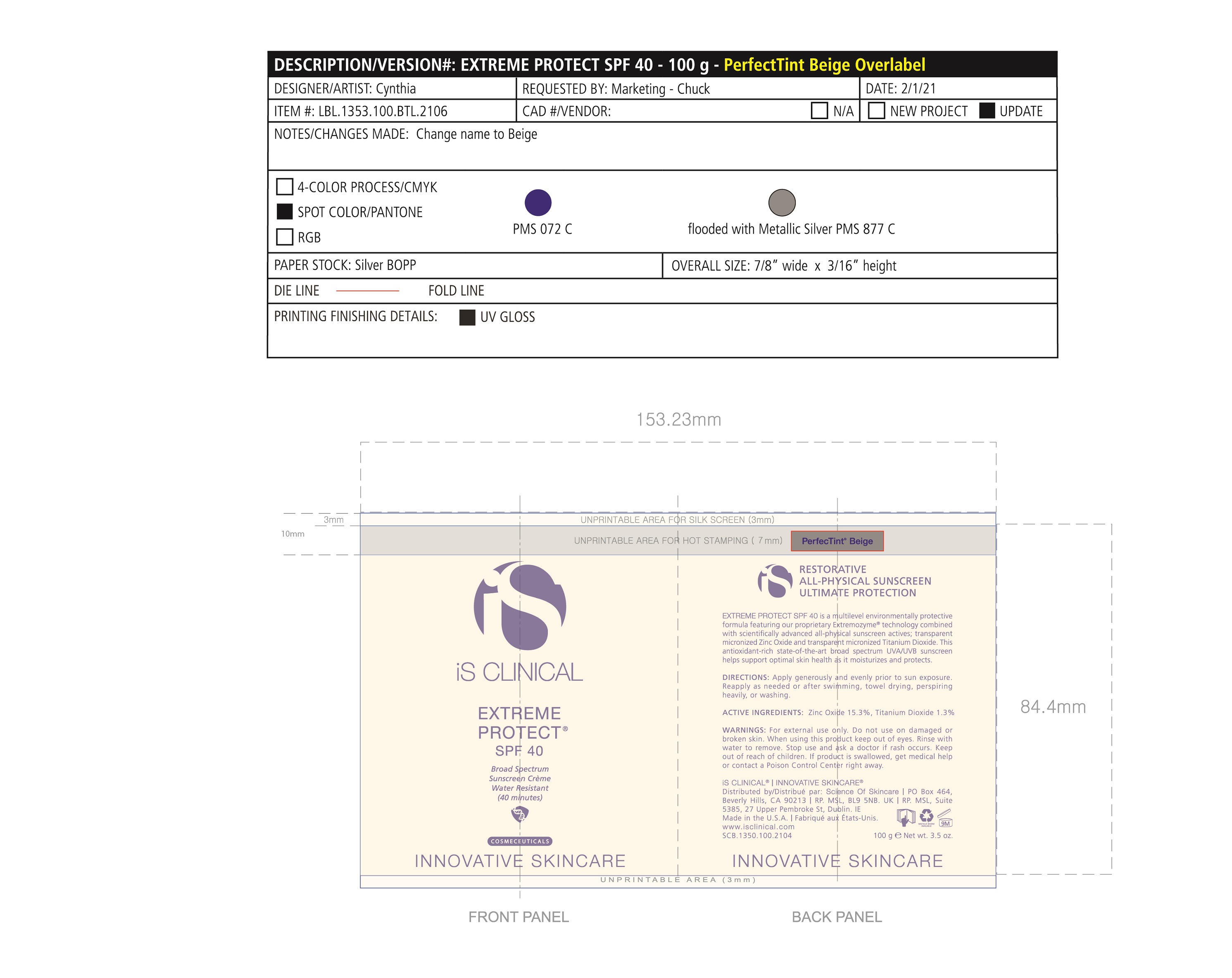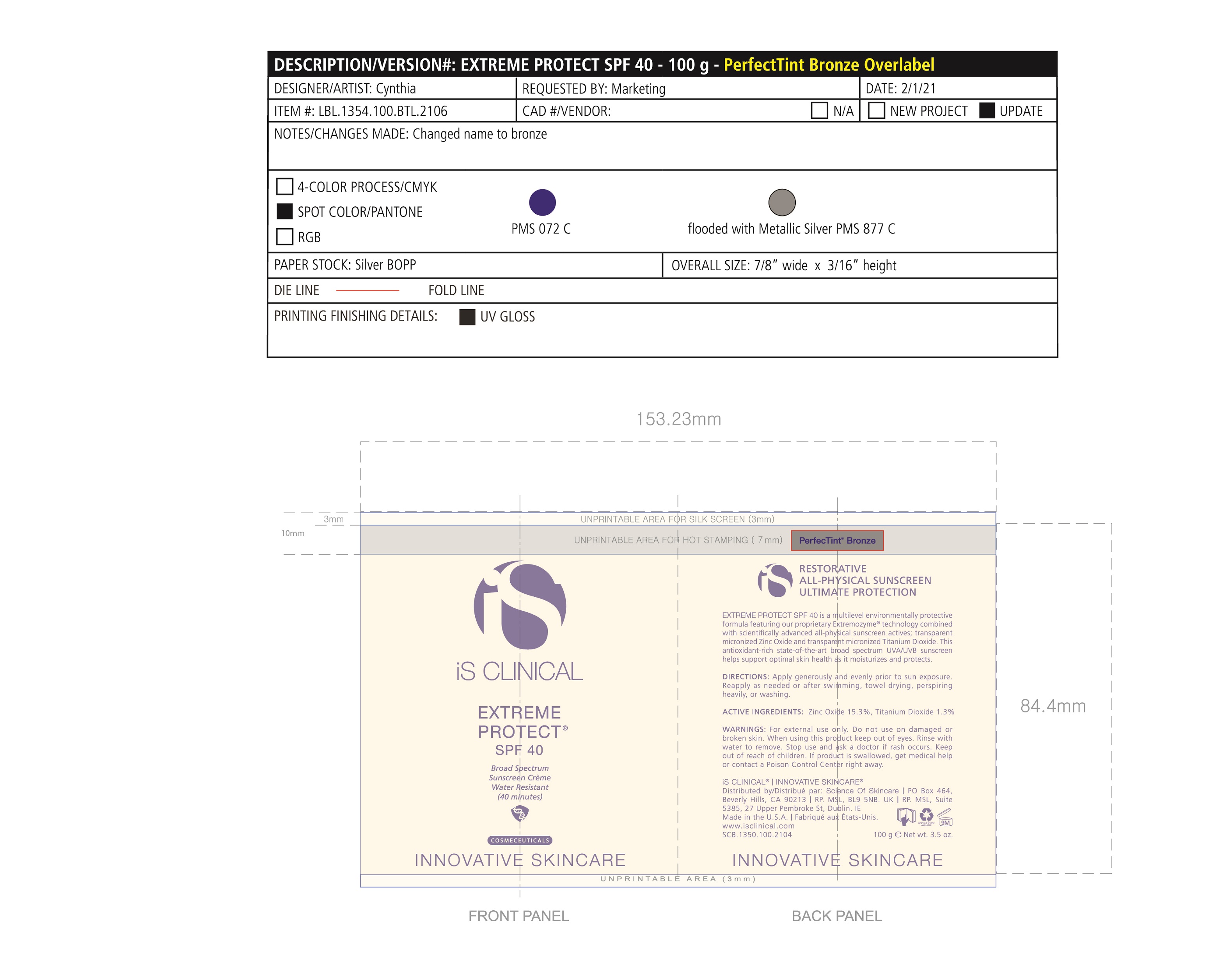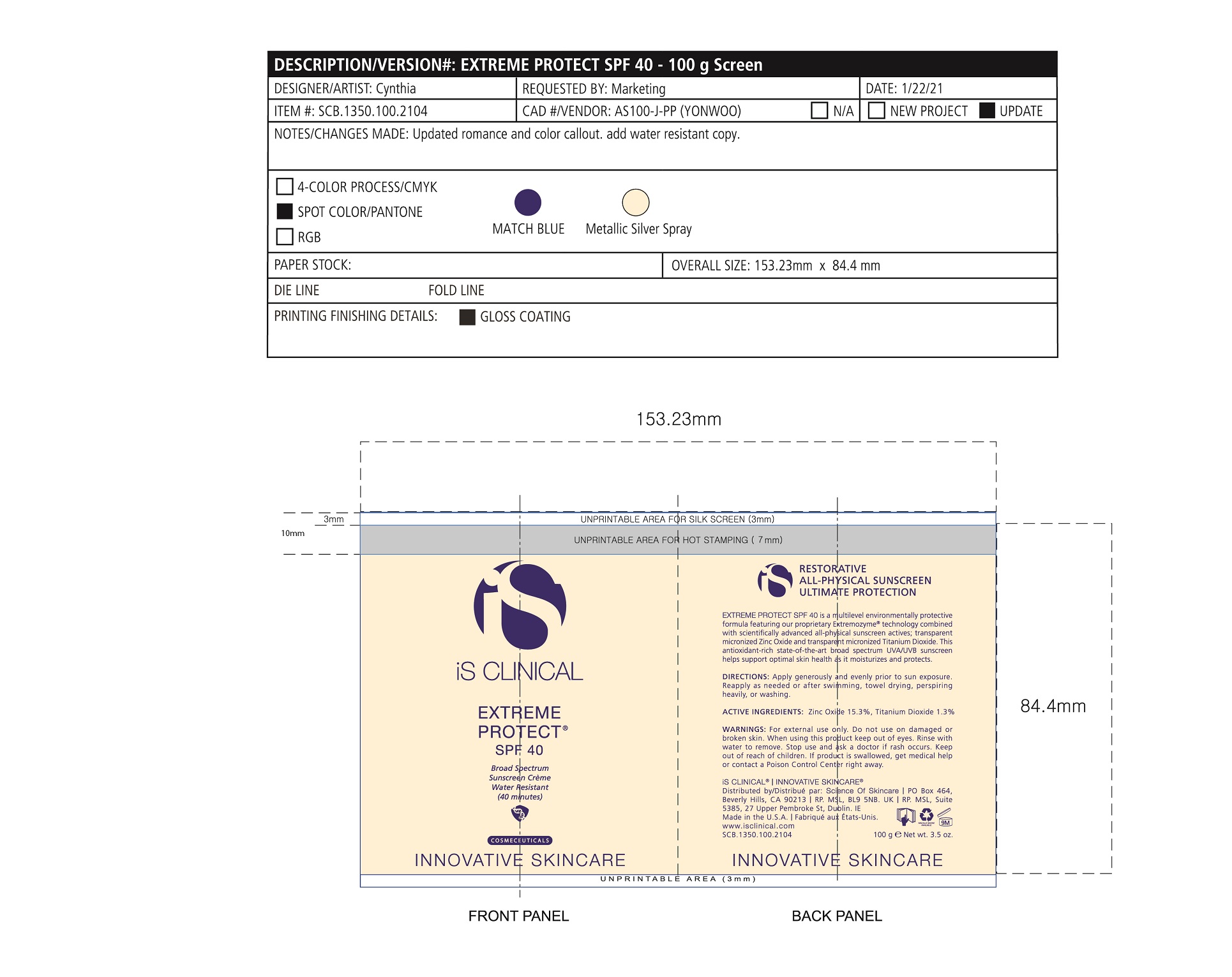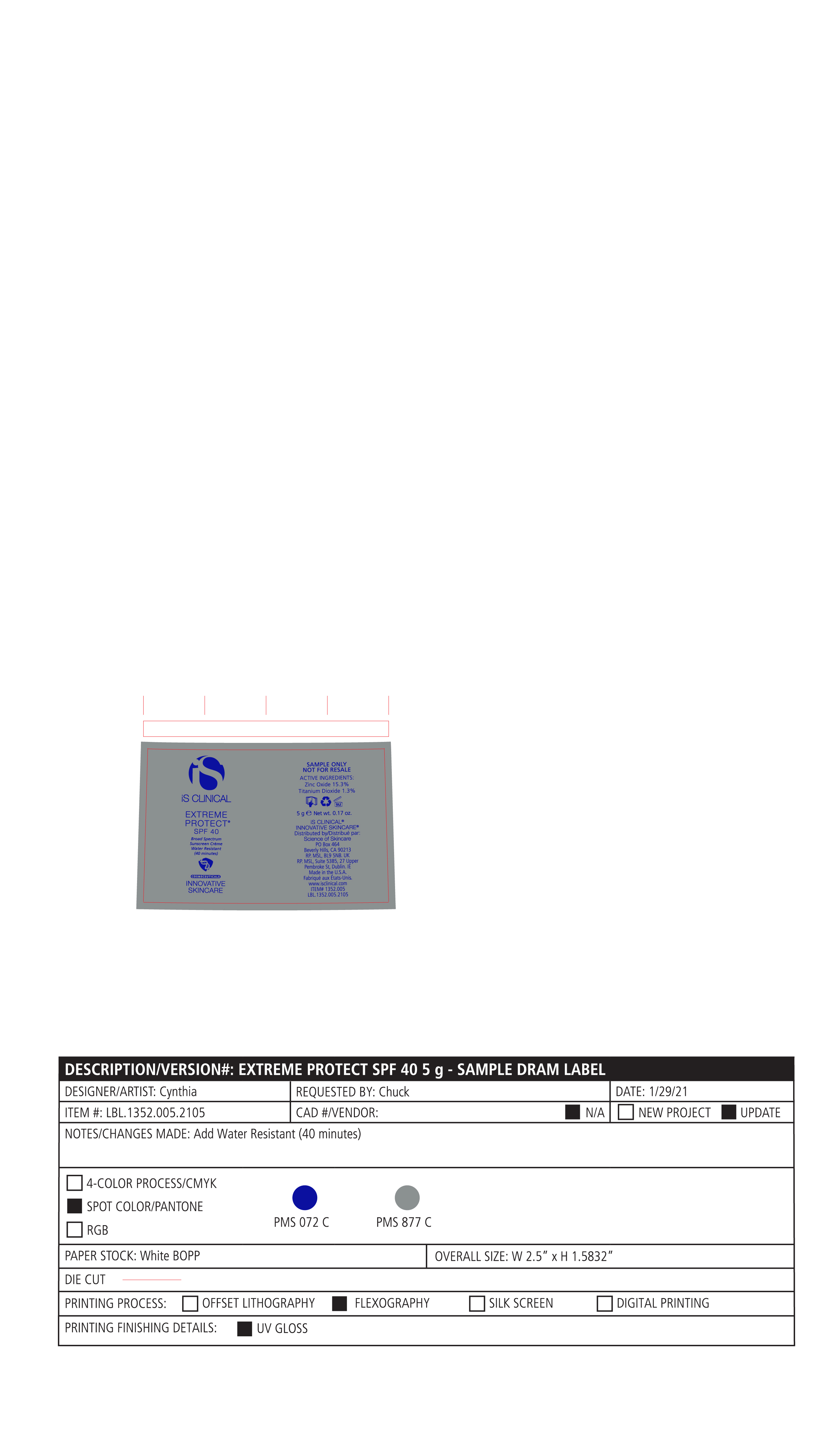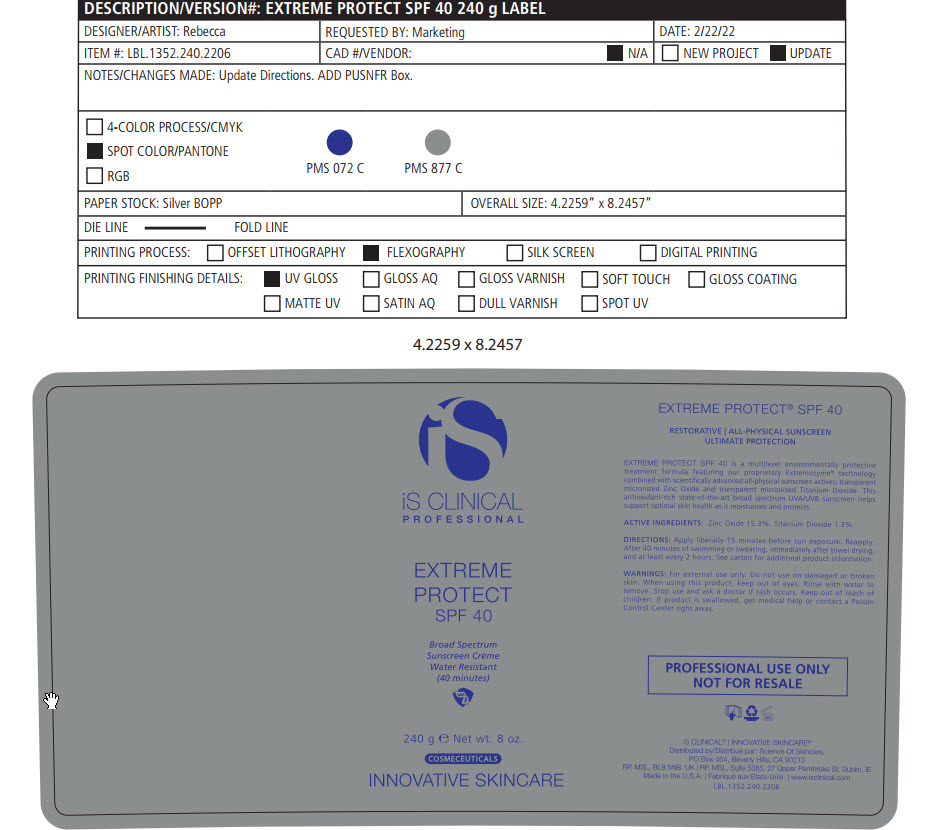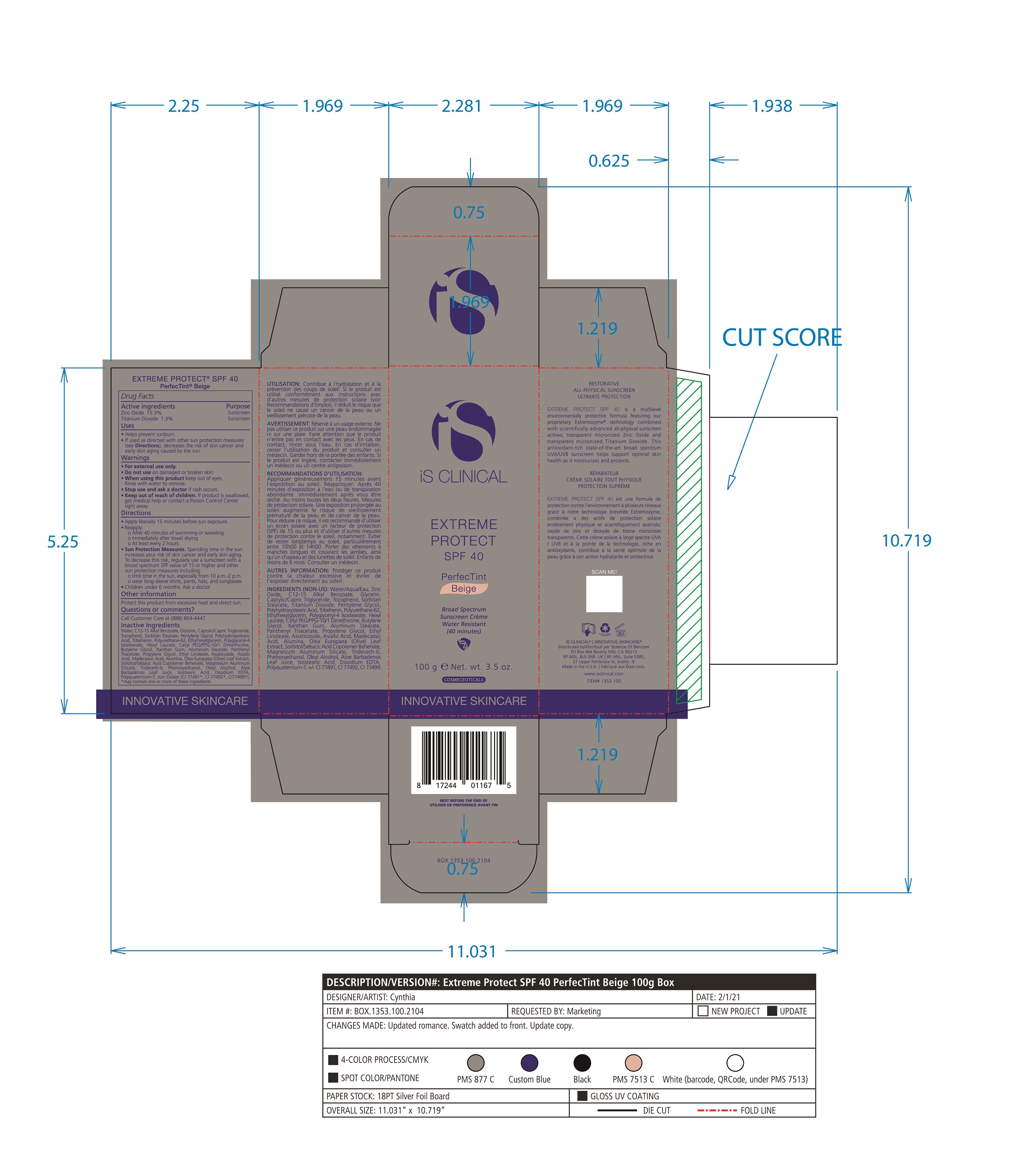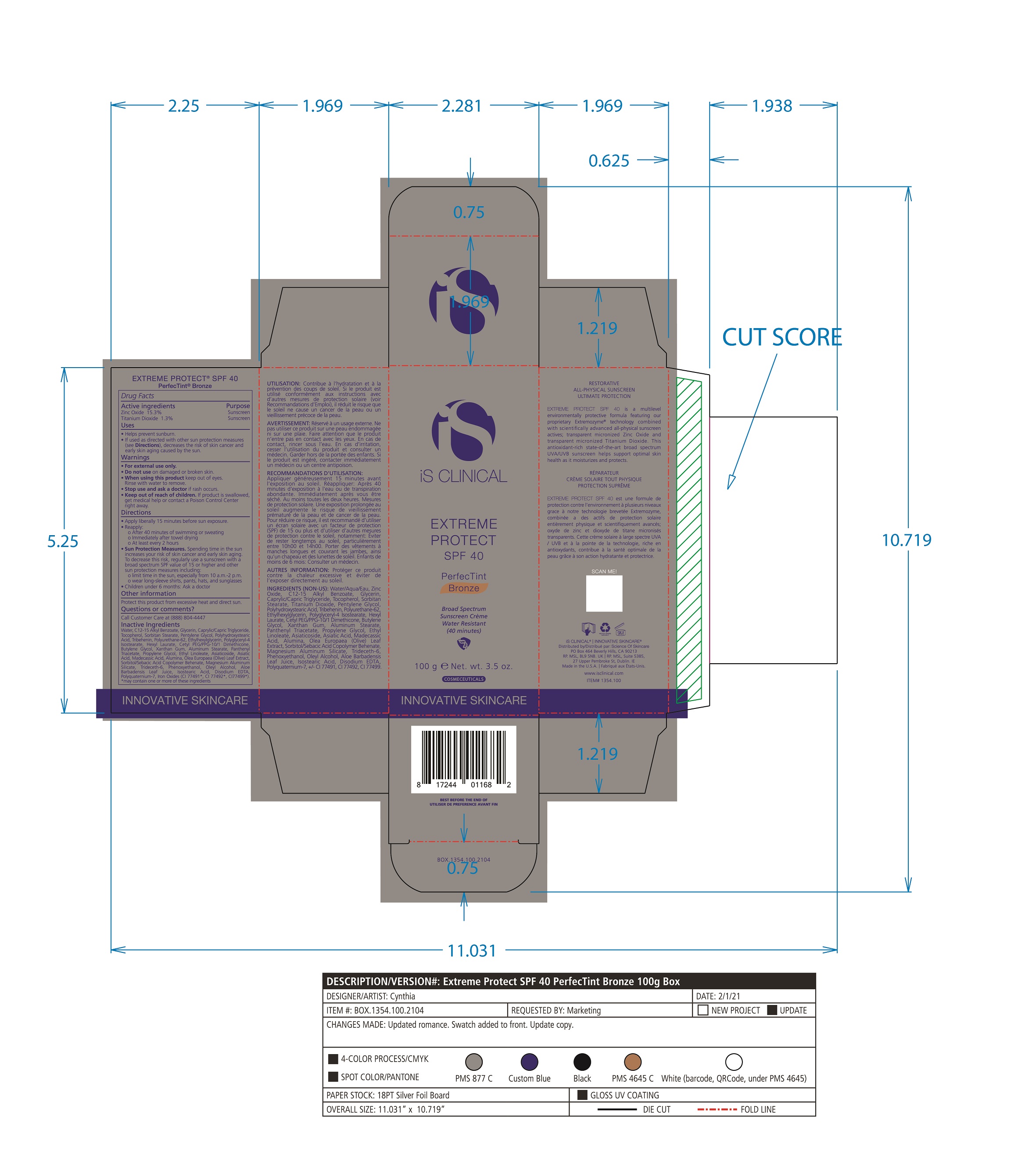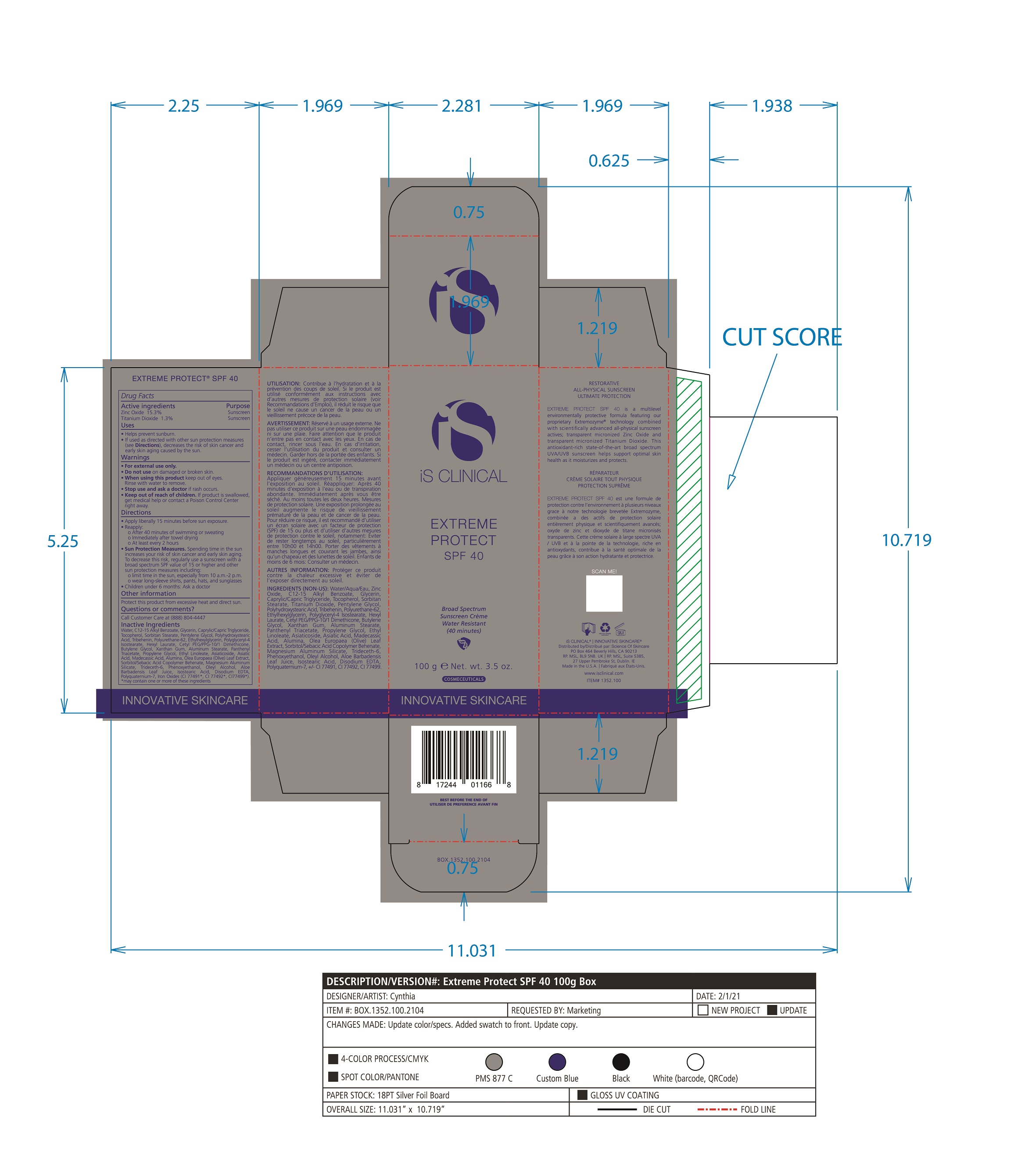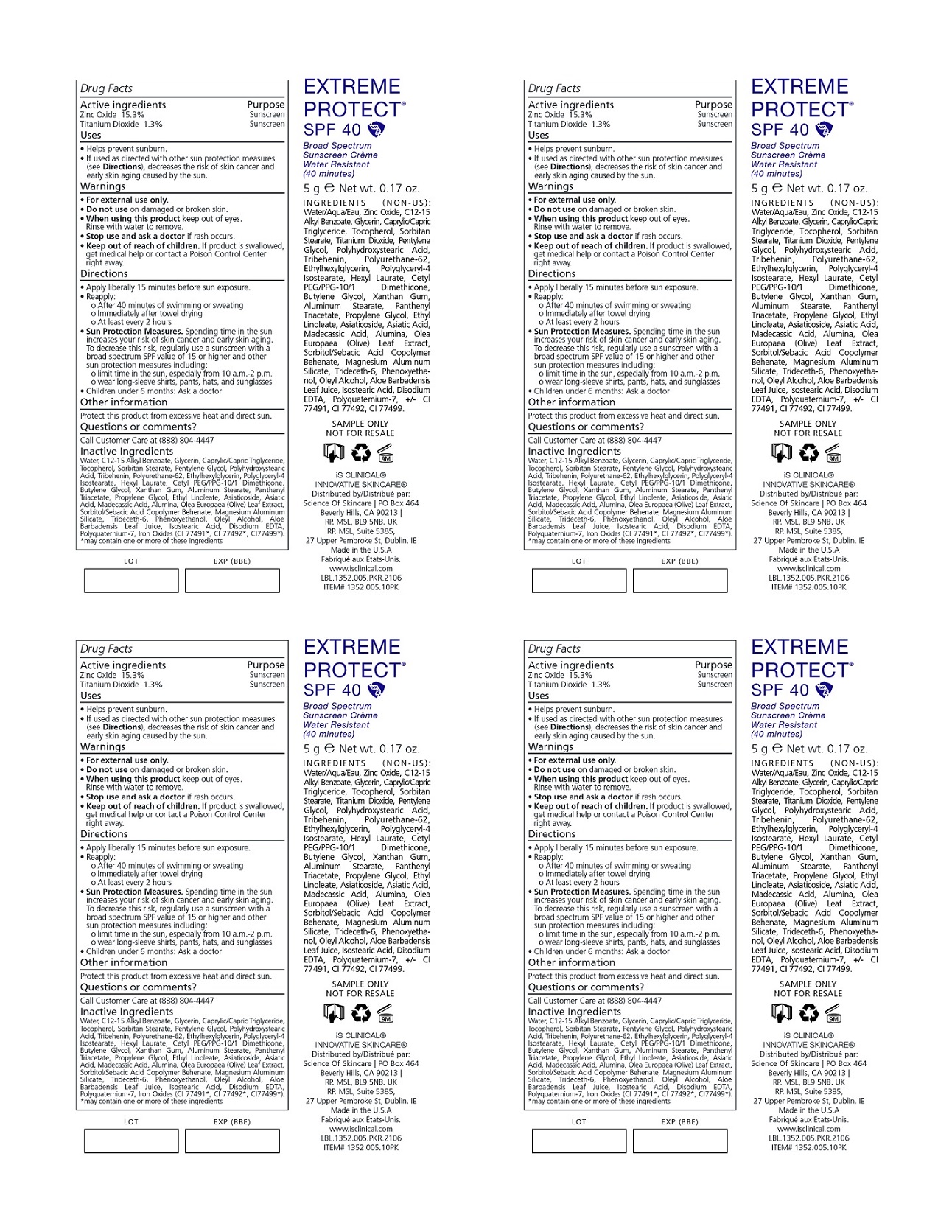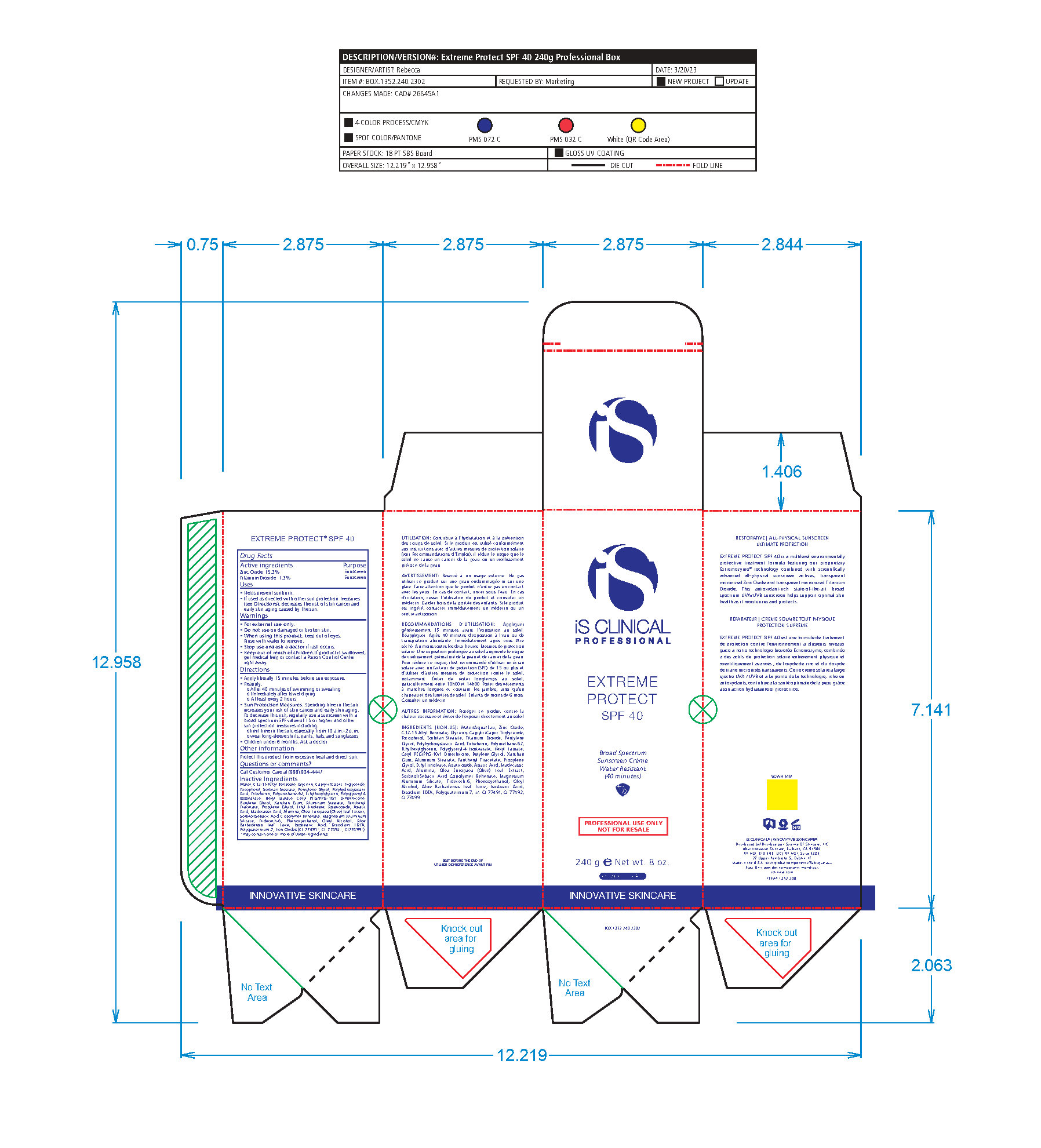 DRUG LABEL: Extreme Protect SPF 40
NDC: 69219-108 | Form: CREAM
Manufacturer: Science of Skincare, LLC.
Category: otc | Type: HUMAN OTC DRUG LABEL
Date: 20250109

ACTIVE INGREDIENTS: TITANIUM DIOXIDE 1.3 g/100 g; ZINC OXIDE 15.3 g/100 g
INACTIVE INGREDIENTS: ETHYLHEXYLGLYCERIN; ALOE VERA LEAF; POLYURETHANE-34 (40 MPA, TENSILE STRENGTH OF FILM AT BREAK); WATER; CETYL PEG/PPG-10/1 DIMETHICONE (HLB 2); XANTHAN GUM; PHENOXYETHANOL; ISOSTEARIC ACID; EDETATE DISODIUM; FERRIC OXIDE RED; POLYQUATERNIUM-7 (70/30 ACRYLAMIDE/DADMAC; 1600 KD); GLYCERIN; MAGNESIUM ALUMINUM SILICATE; OLEYL ALCOHOL; MADECASSIC ACID; DIMETHICONE 100; FERRIC OXIDE YELLOW; CAPRYLOYL GLYCERIN/SEBACIC ACID COPOLYMER (2000 MPA.S); FERROSOFERRIC OXIDE; PANTHENOL TRIACETATE, (+)-; ETHYL LINOLEATE; ASIATICOSIDE; ALKYL (C12-15) BENZOATE; MEDIUM-CHAIN TRIGLYCERIDES; TOCOPHEROL; SORBITAN MONOSTEARATE; HEXYL LAURATE; BUTYLENE GLYCOL; PENTYLENE GLYCOL; POLYGLYCERYL-4 ISOSTEARATE; ALUMINUM STEARATE; ALUMINUM OXIDE; TRIDECETH-6; PROPYLENE GLYCOL; ASIATIC ACID; TRIBEHENIN; OLEA EUROPAEA LEAF; POLYHYDROXYSTEARIC ACID (2300 MW)

Extreme Protect SPF 40

ACTIVE INGREDIENT

Zinc Oxide: 15.3%

Titanium Dioxide: 1.3%

PURPOSE

Sunscreen

INDICATIONS AND USAGE

Helps prevent sunburn.

If used as directed with other sun protection measures(see Directions), decreases the risk of skin cancer and early skin aging caused by the sun.

WARNINGS

For external use only.

Do not use on damaged or broken skin

When using this product keep out of eyes. Rinse with water to remove.

Stop use and ask a doctor if rash occurs.

Keep out of reach of children. If product is swallowed, get medical help or contact a Poison Control Center right away.

DOSAGE AND ADMINISTRATION

Apply liberally 15 minutes before sun exposure.

Reapply:

After 40 minutes of swimming or sweating

Immediately after towel drying

At least every 2 hours

Sun Protection Measures. Spending time in the sun increases your risk of skin cancer and early skin aging. To decrease this risk, regularly use a sunscreen with a broad spectrum SPF value of 15 or higher and other sun protection measures including:

limit time in the sun, especially from 10am - 2pm.

wear long-sleeve shirts, pants, hats, and sunglasses.

OTHER SAFETY INFORMATION

Protect this product from excessive heat and direct sun.

QUESTIONS

Call Customer Care at (888) 804 - 4447

INACTIVE INGREDIENT

Water/Aqua/Eau, Zinc Oxide, C12-15 Alkyl Benzoate, Glycerin, Caprylic Capric Triglycerides, Tocopherol, Sorbitan Stearate, Panthenyl Triacetate, Titanium Dioxide, Pentylene Glycol, Ethyl Linoleate, Polyhydroxystearic Acid, Tribehenin, Polyurethane-62, Ethylhexylglycerin, Polyglyceryl-4 Isostearate, Hexyl Laurate, Cetyl PEG/PPG-10/1 Dimethicone, Butylene Glycol, Oleyl Alcohol, Xanthan Gum, Aluminum Stearate, Propylene Glycol, Asiaticoside, Asiatic Acid, Madecassic Acid, Alumina, Olea Europaea (Olive) Leaf Extract, Sorbitol/Sebacic Acid Copolymer Behenate, Magnesium Aluminum Silicate, Trideceth-6, Phenoxyethanol, Aloe Barbadensis Leaf Juice, Isostearic Acid, Disodium EDTA, Polyquaternium-7, +/- CI 77491, CI 77492, CI 77499 *May contain one or more of these ingredients